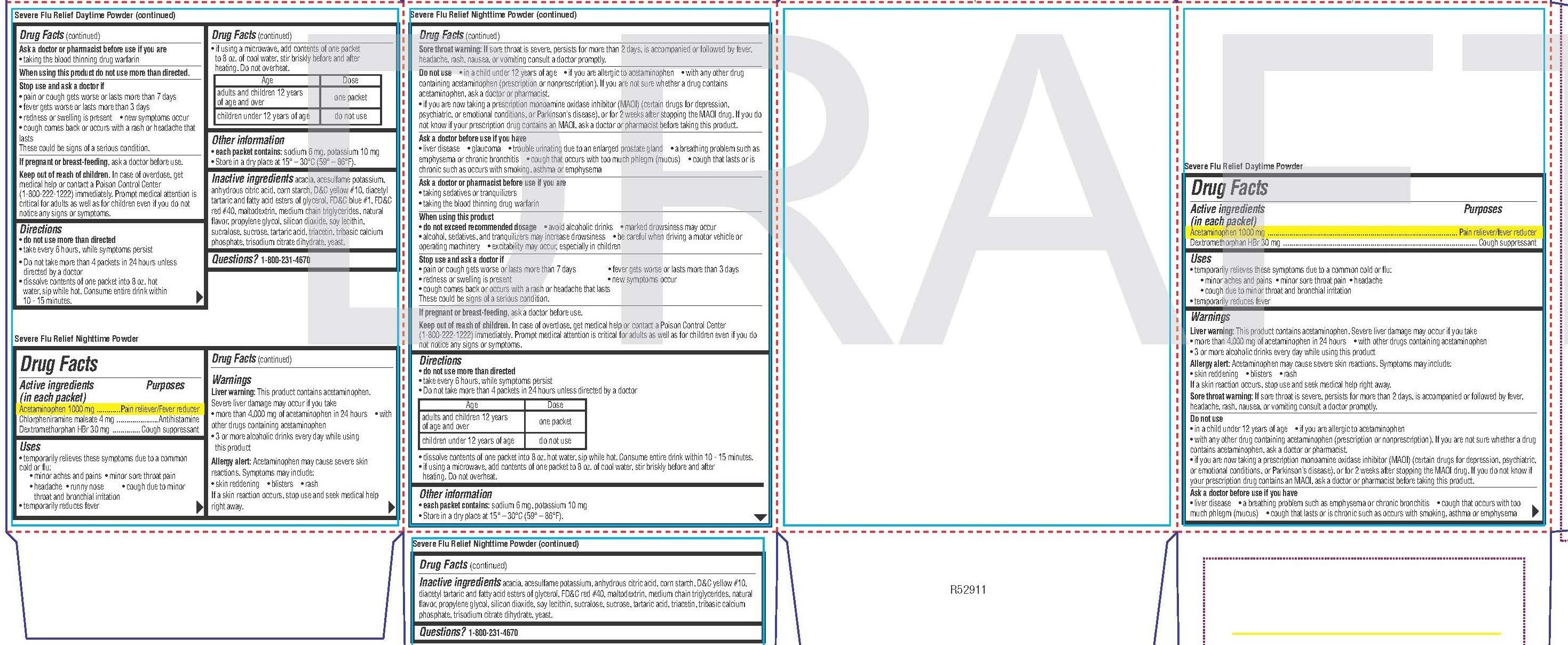 DRUG LABEL: Acetaminophen, Dextromethorphan HBr, Chlorpheniramine Maleate
NDC: 51316-609 | Form: KIT | Route: ORAL
Manufacturer: CVS Pharmacy, Inc
Category: otc | Type: HUMAN OTC DRUG LABEL
Date: 20251021

ACTIVE INGREDIENTS: DEXTROMETHORPHAN HYDROBROMIDE 30 mg/1 1; ACETAMINOPHEN 1000 mg/1 1; DEXTROMETHORPHAN HYDROBROMIDE 30 mg/1 1; CHLORPHENIRAMINE MALEATE 4 mg/1 1; ACETAMINOPHEN 1000 mg/1 1
INACTIVE INGREDIENTS: TRIBASIC CALCIUM PHOSPHATE; TRISODIUM CITRATE DIHYDRATE; STARCH, CORN; FD&C BLUE NO. 1; MALTODEXTRIN; PROPYLENE GLYCOL; DIACETYLTARTARIC AND FATTY ACID ESTERS OF GLYCEROL; YEAST; SUCROSE; TRIACETIN; SILICON DIOXIDE; SUCRALOSE; ACACIA; ACESULFAME POTASSIUM; ANHYDROUS CITRIC ACID; D&C YELLOW NO. 10; SOYBEAN LECITHIN; FD&C RED NO. 40; MEDIUM-CHAIN TRIGLYCERIDES; TARTARIC ACID; ANHYDROUS CITRIC ACID; DIACETYLTARTARIC AND FATTY ACID ESTERS OF GLYCEROL; PROPYLENE GLYCOL; STARCH, CORN; SILICON DIOXIDE; YEAST; MALTODEXTRIN; SUCROSE; TARTARIC ACID; TRISODIUM CITRATE DIHYDRATE; ACACIA; FD&C RED NO. 40; ACESULFAME POTASSIUM; D&C YELLOW NO. 10; TRIBASIC CALCIUM PHOSPHATE; MEDIUM-CHAIN TRIGLYCERIDES; SUCRALOSE; TRIACETIN; SOYBEAN LECITHIN

6183-Combo Pack CVS

Day Time Powder

Drug Facts

Active ingredients (in each packet)
Acetaminophen 1000 mg
Dextromethorphan HBr 30 mg

Purposes
Pain reliever/fever reducer
Cough suppressant

Uses

• temporarily relieves these symptoms due to a common cold or flu:
• minor aches and pains • minor sore throat pain • headache
• cough due to minor throat and bronchial irritation
• temporarily reduces fever

WARNINGS

Liver warning: This product contains acetaminophen. Severe liver damage may occur if you take
• more than 4,000 mg of acetaminophen in 24 hours

• with other drugs containing acetaminophen
• 3 or more alcoholic drinks every day while using this product
Allergy alert: Acetaminophen may cause severe skin reactions. Symptoms may include:
• skin reddening • blisters • rash
If a skin reaction occurs, stop use and seek medical help right away.
Sore throat warning: If sore throat is severe, persists for more than 2 days, is accompanied or followed by fever, headache, rash, nausea, or vomiting consult a doctor promptly.

DO NOT USE

• in a child under 12 years of age

• if you are allergic to acetaminophen
• with any other drug containing acetaminophen (prescription or nonprescription). If you are not sure whether a drug contains acetaminophen, ask a doctor or pharmacist.
• if you are now taking a prescription monoamine oxidase inhibitor (MAOI) (certain drugs for depression, psychiatric, or emotional conditions, or Parkinson’s disease), or for 2 weeks after stopping the MAOI drug. If you do not know if your prescription drug contains an MAOI, ask a doctor or pharmacist before taking this product.

Ask a doctor before use if you have
• liver disease

• a breathing problem such as emphysema or chronic bronchitis

• cough that occurs with too much phlegm (mucus)

• cough that lasts or is chronic such as occurs with smoking, asthma or emphysema

Ask a doctor or pharmacist before use if you are
• taking the blood thinning drug warfarin

When using this product do not use more than directed.

Stop use and ask a doctor if
• pain or cough gets worse or lasts more than 7 days
• fever gets worse or lasts more than 3 days
• redness or swelling is present

• new symptoms occur
• cough comes back or occurs with a rash or headache that lasts
These could be signs of a serious condition.

PREGNANCY OR BREAST FEEDING

If pregnant or breast-feeding, ask a doctor before use.

Keep out of reach of children.

OVERDOSAGE

In case of overdose, get medical help or contact a Poison Control Center (1-800-222-1222) immediately. Prompt medical attention is
critical for adults as well as for children even if you do not notice any signs or symptoms.

Directions

• do not use more than directed
• take every 6 hours, while symptoms persist
• Do not take more than 4 packets in 24 hours unless directed by a doctor
• dissolve contents of one packet into 8 oz. hot water, sip while hot. Consume entire drink within 10 - 15 minutes.

• if using a microwave, add contents of one packet to 8 oz. of cool water, stir briskly before and after heating. Do not overheat.

Age | Dose
adults and children 12 years of age and over | one packet
children under 12 years of age | do not use

Other information

• each packet contains: sodium 6 mg, potassium 10 mg
• Store in a dry place at 15° – 30°C (59° – 86°F).

INACTIVE INGREDIENT

acacia, acesulfame potassium, anhydrous citric acid, corn starch, D&C yellow #10, diacetyl tartaric and fatty acid esters of glycerol, FD&C blue #1, FD&C red #40, maltodextrin, medium chain triglycerides, natural flavor, propylene glycol, silicon dioxide, soy lecithin,
sucralose, sucrose, tartaric acid, triacetin, tribasic calcium phosphate, trisodium citrate dihydrate, yeast.

Nighttime Powder

Drug Facts

Active ingredients (in each packet)
Acetaminophen 1000 mg
Chlorpheniramine maleate 4 mg
Dextromethorphan HBr 30 mg

Purposes
Pain reliever/Fever reducer
Antihistamine
Cough suppressant

Uses

• temporarily relieves these symptoms due to a common cold or flu:
• minor aches and pains • minor sore throat pain
• headache • runny nose • cough due to minor throat and bronchial irritation
• temporarily reduces fever

WARNINGS

Liver warning: This product contains acetaminophen. Severe liver damage may occur if you take
• more than 4,000 mg of acetaminophen in 24 hours

• with other drugs containing acetaminophen
• 3 or more alcoholic drinks every day while using this product
Allergy alert: Acetaminophen may cause severe skin reactions. Symptoms may include:
• skin reddening • blisters • rash
If a skin reaction occurs, stop use and seek medical help right away.

Sore throat warning: If sore throat is severe, persists for more than 2 days, is accompanied or followed by fever, headache, rash, nausea, or vomiting consult a doctor promptly

Do not use

• in a child under 12 years of age

• if you are allergic to acetaminophen

• with any other drug containing acetaminophen (prescription or nonprescription). If you are not sure whether a drug contains acetaminophen, ask a doctor or pharmacist.
• if you are now taking a prescription monoamine oxidase inhibitor (MAOI) (certain drugs for depression, psychiatric, or emotional conditions, or Parkinson’s disease), or for 2 weeks after stopping the MAOI drug. If you do not know if your prescription drug contains an MAOI, ask a doctor or pharmacist before taking this product.

Ask a doctor before use if you have
• liver disease

• glaucoma

• trouble urinating due to an enlarged prostate gland

• a breathing problem such as emphysema or chronic bronchitis

• cough that occurs with too much phlegm (mucus) • cough that lasts or is chronic such as occurs with smoking, asthma or emphysema

Ask a doctor or pharmacist before use if you are
• taking sedatives or tranquilizers
• taking the blood thinning drug warfarin

When using this product
• do not exceed recommended dosage

• avoid alcoholic drinks

• marked drowsiness may occur
• alcohol, sedatives, and tranquilizers may increase drowsiness

• be careful when driving a motor vehicle or operating machinery

• excitability may occur, especially in children

Stop use and ask a doctor if
• pain or cough gets worse or lasts more than 7 days

• fever gets worse or lasts more than 3 days
• redness or swelling is present

• new symptoms occur
• cough comes back or occurs with a rash or headache that lasts

These could be signs of a serious condition.

PREGNANCY OR BREAST FEEDING

If pregnant or breast-feeding, ask a doctor before use.

Keep out of reach of children.

OVERDOSAGE

In case of overdose, get medical help or contact a Poison Control Center (1-800-222-1222) immediately. Prompt medical attention is critical for adults as well as for children even if you do not notice any signs or symptoms.

Directions

• do not use more than directed
• take every 6 hours, while symptoms persist
• Do not take more than 4 packets in 24 hours unless directed by a doctor

• dissolve contents of one packet into 8 oz. hot water, sip while hot. Consume entire drink within 10 - 15 minutes.
• if using a microwave, add contents of one packet to 8 oz. of cool water, stir briskly before and after heating. Do not overheat.

Age | Dose
adults and children 12 years of age and over | one packet
children under 12 years of age | do not use

Other information

• each packet contains: sodium 6 mg, potassium 10 mg
• Store in a dry place at 15° – 30°C (59° – 86°F).

INACTIVE INGREDIENT

acacia, acesulfame potassium, anhydrous citric acid, corn starch, D&C yellow #10, diacetyl tartaric and fatty acid esters of glycerol, FD&C red #40, maltodextrin, medium chain triglycerides, natural flavor, propylene glycol, silicon dioxide, soy lecithin, sucralose, sucrose, tartaric acid, triacetin, tribasic calcium phosphate, trisodium citrate dihydrate, yeast.

Questions? 1-800-231-4670